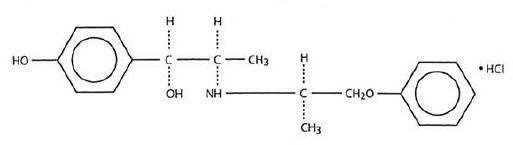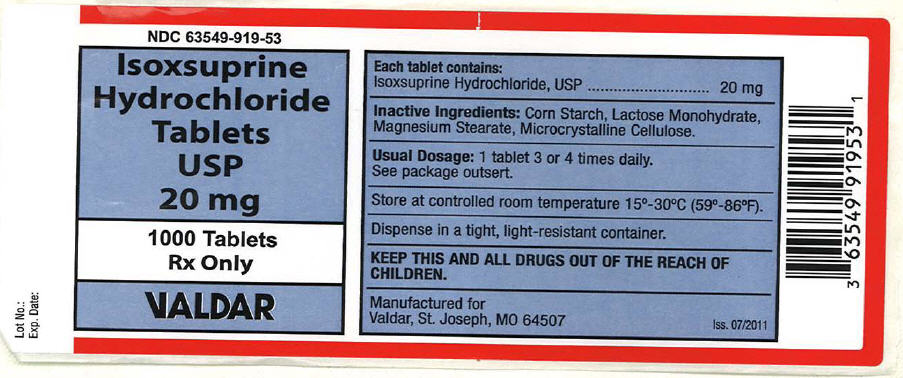 DRUG LABEL: ISOXSUPRINE HYDROCHLORIDE
NDC: 63549-919 | Form: TABLET
Manufacturer: Vedco dba Valdar
Category: prescription | Type: HUMAN PRESCRIPTION DRUG LABEL
Date: 20120102

ACTIVE INGREDIENTS: isoxsuprine hydrochloride 20 mg/1 1
INACTIVE INGREDIENTS: Lactose Monohydrate; Magnesium Stearate; Cellulose, Microcrystalline; Starch, Corn

Isoxsuprine Hydrochloride Tablets, USP

Rx Only

DESCRIPTION

Each tablet taken orally contains Isoxsuprine Hydrochloride, USP with the following chemical structure:

C18 H23 NO3 • HCl

p-Hydroxy-α[1-[(methyl-2-phenoxy-ethyl)amino]ethyl]benzyl alcohol hydrochloride.

QUANTITATIVE INGREDIENT INFORMATION

Each tablet taken orally contains 20mg Isoxsuprine Hydrochloride.

PHARMACOLOGICAL CLASS

Peripheral Vasodilator

INDICATIONS

Based on a review of this drug by the National Academy of Sciences-National Research and/or other information, the FDA has classified the indications as follows:

Possibly Effective

1. For the relief of symptoms associated with cerebrovascular insufficiency.
2. In peripheral vascular disease of arteriosclerosis obliterans, thromboangitis obliterans (Buerger's disease) and Raynaud's disease.

Final classification of the less-than-effective indications requires further investigation.

CONTRAINDICATIONS

There are no known contraindications to oral use when administered in recommended doses.

Isoxsuprine Hydrochloride, USP should not be given immediately postpartum or in the presence of arterial bleeding.

PRECAUTIONS

Pediatric Use

Safety and effectiveness in pediatric patients has not been established.

ADVERSE REACTIONS

On rare occasion oral administration of the drug has been associated in time with the occurrence of hypotension, tachycardia, chest pain, nausea, vomiting, dizziness, abdominal distress, and severe rash. If rash appears, the drug should be discontinued.

Although available evidence suggests a temporal association of these reactions with Isoxsuprine Hydrochloride, a causal relationship can be neither confirmed nor refuted.

Beta Adrenergic receptor stimulants such as Isoxsuprine Hydrochloride have been used to inhibit pre-term labor.

Maternal and fetal tachycardia may occur under such use.

Hypocalcemia, hypoglycemia, hypotension and ileus have been reported to occur in infants whose mothers received Isoxsuprine Hydrochloride. Pulmonary edema has been reported in mothers treated with beta stimulants. Isoxsuprine Hydrochloride is neither approved nor recommended for use in the treatment of premature labor.

DOSAGE AND ADMINISTRATION

Oral: 10 to 20 mg, three or four times daily.

HOW SUPPLIED

Isoxsuprine HCl tablets, USP 20 mg

Bottles of 1000 NDC 63549-919-53

COMPOSITION

Isoxsuprine HCl 20mg tablets: These tablets contain the following inactive ingredients: corn starch, lactose monohydrate, magnesium stearate (vegetable), microcrystalline cellulose.

Manufactured For:
Valdar
St. Joseph, MO 64507

PRINCIPAL DISPLAY PANEL - 20 mg Tablet Bottle Label

NDC 63549-919-53

Isoxsuprine
Hydrochloride
Tablets
USP
20 mg

1000 Tablets

Rx Only

VALDAR